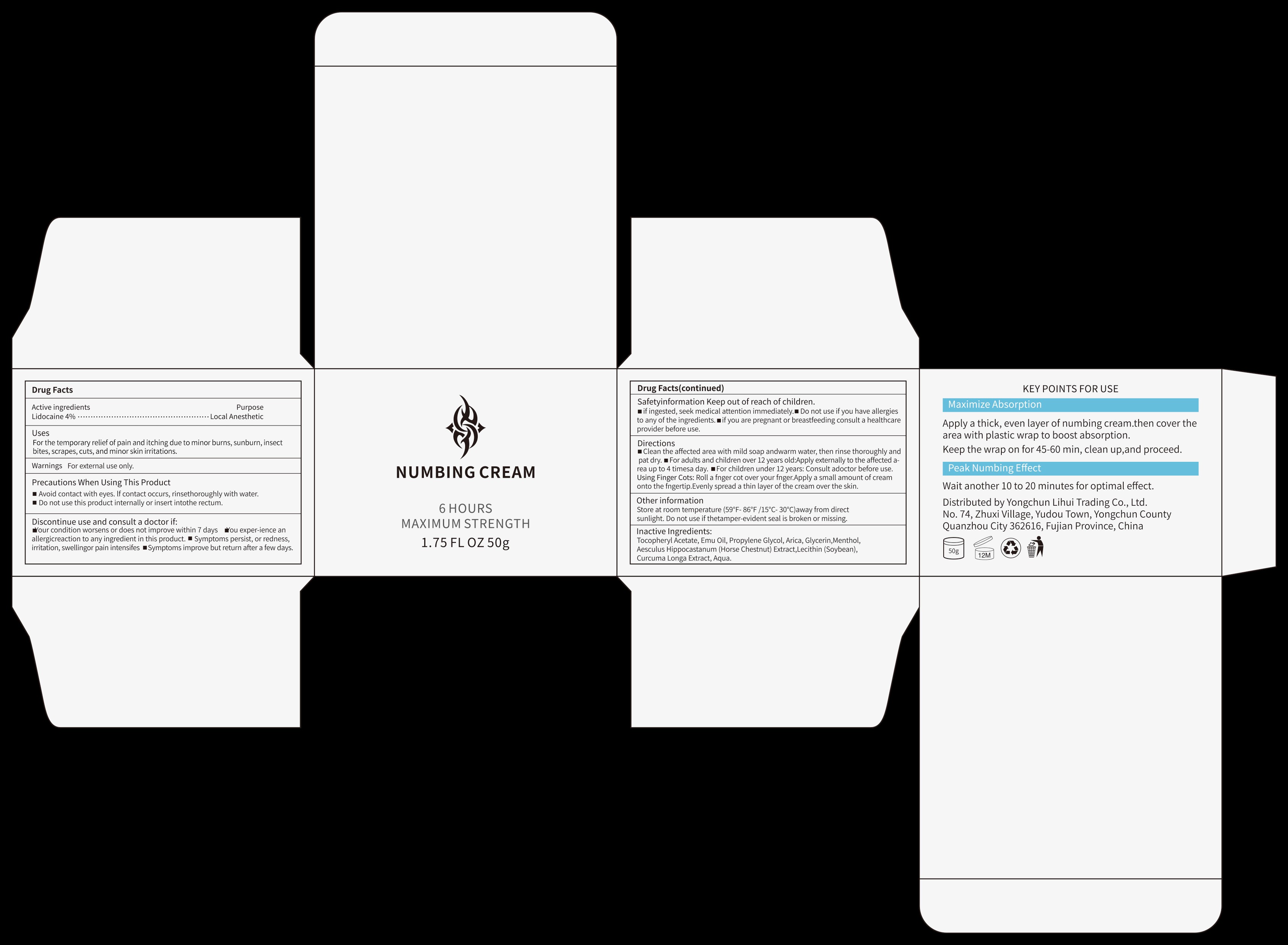 DRUG LABEL: NUMBING CREAMS
NDC: 85881-001 | Form: CREAM
Manufacturer: Yongchun Lihui Trading Co., Ltd.
Category: otc | Type: HUMAN OTC DRUG LABEL
Date: 20260227

ACTIVE INGREDIENTS: LIDOCAINE 4 g/100 g
INACTIVE INGREDIENTS: MENTHOL; HYDROGENATED SOYBEAN LECITHIN; PROPYLENE GLYCOL; GLYCERIN; CURCUMA LONGA (TURMERIC) ROOT; AQUA; ARNICA MONTANA FLOWER; .ALPHA.-TOCOPHEROL ACETATE; EMU OIL; HORSE CHESTNUT

ACTIVE INGREDIENT

Lidocaine 4%

PURPOSE

UsesFor the temporary relief of pain and itching due to minor burns, sunburn, insectbites,scrapes, cuts, and minor skin irritations.

Warnings For external use only.

KEEP OUT OF REACH OF CHILDREN

Safetyinformation Keep out of reach of children.if ingested, seek medical attention immediately. Do not use if you have allergiesto any of the ingredients.m if you are pregnant or breastfeeding consult a healthcareprovider before use.

INACTIVE INGREDIENT

Inactive Ingredients:Tocopheryl Acetate, Emu Oil, Propylene Glycol, Arica, Glycerin,MentholAesculus Hippocastanum (Horse Chestnut) Extract,Lecithin (Soybean),Curcuma Longa Extract, Aqua.

INDICATIONS AND USAGE

DirectionsClean the affected area with mild soap andwarm water, then rinse thoroughly andpat dry. For adults and children over 12 years old:Apply externally to the affected a-rea up to 4 timesa day. For children under 12 years: Consult adoctor before use.Using Finger Cots: Roll a fnger cot over your fnger.Apply a small amount of creamonto the fngertip.Evenly spread a thin layer of the cream over the skin.

STOP USE

Discontinue use and consult a doctor if:Your condition worsens or does not improve within 7 days ou exper-ience anallergicreaction to any ingredient in this product.Symptoms persist, or redness.irritation, swellingor pain intensifes Symptoms improve but return after a few days.

DOSAGE AND ADMINISTRATION

Apply externally to the affected a-rea up to 4 timesa day